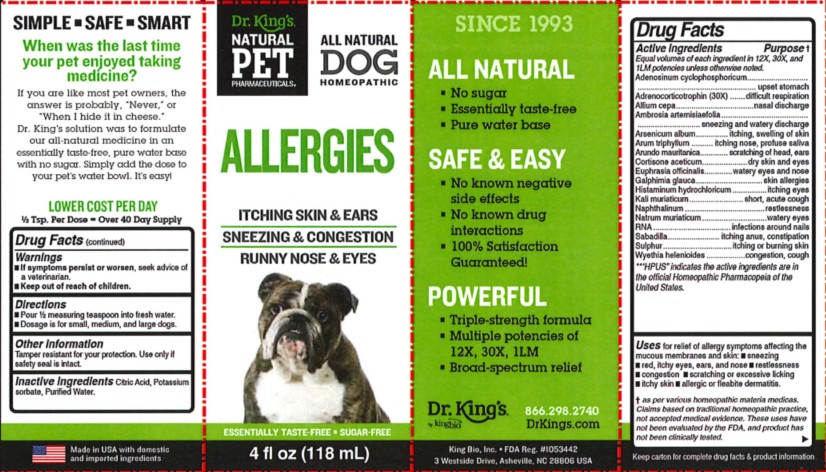 DRUG LABEL: Allergies
NDC: 57955-4809 | Form: LIQUID
Manufacturer: King Bio Inc.
Category: homeopathic | Type: OTC ANIMAL DRUG LABEL
Date: 20250502

ACTIVE INGREDIENTS: ADENOSINE CYCLIC PHOSPHATE 12 [hp_X]/118 mL; CORTICOTROPIN 30 [hp_X]/118 mL; ONION 12 [hp_X]/118 mL; AMBROSIA ARTEMISIIFOLIA WHOLE 12 [hp_X]/118 mL; ARSENIC TRIOXIDE 12 [hp_X]/118 mL; ARISAEMA TRIPHYLLUM ROOT 12 [hp_X]/118 mL; ARUNDO PLINIANA ROOT 12 [hp_X]/118 mL; CORTISONE ACETATE 12 [hp_X]/118 mL; EUPHRASIA STRICTA 12 [hp_X]/118 mL; GALPHIMIA GLAUCA FLOWERING TOP 12 [hp_X]/118 mL; HISTAMINE DIHYDROCHLORIDE 12 [hp_X]/118 mL; POTASSIUM CHLORIDE 12 [hp_X]/118 mL; NAPHTHALENE 12 [hp_X]/118 mL; SODIUM CHLORIDE 12 [hp_X]/118 mL; SACCHAROMYCES CEREVISIAE RNA 12 [hp_X]/118 mL; SCHOENOCAULON OFFICINALE SEED 12 [hp_X]/118 mL; SULFUR 12 [hp_X]/118 mL; WYETHIA HELENIOIDES ROOT 12 [hp_X]/118 mL
INACTIVE INGREDIENTS: ANHYDROUS CITRIC ACID; POTASSIUM SORBATE; WATER

Allergies

Warnings

If symptoms persist or worsen, seek advice of
a veterinarian.

Keep out of reach of children.

Directions

Pour ½ measuring teaspoon into fresh water.

Dosage is for small, medium, and large dogs.

Other information

Tamper resistant for your protection.

Use only if safety seal is intact.

This product has not been clinically tested.

Questions? Call 866.298.2740

King Bio, Inc. 3 Westside Drive

Asheville, NC 2806 USA

FDA Reg. #1053442

For the latest product information and instructions: www.DrKings.com

Keep out of reach of children.

Ingredients

Equal volumes of each HPUS** ingredient in 12X,
30X, and 1LM potencies.

Adenosinum cyclophosphoricum, Adrenocorticotrophin (30X), Allium cepa, Ambrosia artemisiaefolia, Arsenicum album, Arum triphyllum, Arundo mauritanica, Cortisone aceticum, Euphrasia officinalis, Galphimia glauca, Histaminum hydrochloricum, Kali muriaticum, Naphthalinum, Natrum muriaticum, RNA, Sabadilla, Sulphur, and Wyethia helenioides.

**“HPUS” indicates the active ingredients are in the official Homeopathic Pharmacopeia of the United States.

Uses

Uses for relief of allergy symptoms affecting the mucous membranes and skin

- sneezing
- red, itchy eyes, ears, and nose
- restlessness
- congestion

- scratching or excessive licking

- itchy skin
- allergic or fleabite dermatitis

† as per various homeopathic materia medicas.
Claims based on traditional homeopathic practice,
not accepted medical evidence. These uses have
not been evaluated by the FDA, and product has
not been clinically tested

Inactive ingredients

Citric Acid, Potassium sorbate, and Purified Water.

Active ingredients Purpose †
Equal volumes of each HPUS** ingredient in 12X,
30X, and 1LM potencies.

Adenosinum cyclophosphoricum..............upset stomach

Adrenocorticotrophin (30X) ..............difficult respiration

Allium cepa .........................................nasal discharge

Ambrosia artemisiaefolia ...sneezing and water discharge

Arsenicum album ......................itching, swelling of skin

Arum triphyllum ...................itching nose, profuse saliva

Arundo mauritanica ..................scratching of head, ears

Cortisone aceticum ............................dry skin and eyes

Euphrasia officinalis ......................watery eyes and nose

Galphimia glauca ......................................skin allergies

Histaminum hydrochloricum ........................itching eyes

Kali muriaticum ................................short, acute cough

Naphthalinum ............................................restlessness

Natrum muriaticum ....................................watery eyes

RNA ...........................................infections around nails

Sabadilla ................................inching anus, constipation

Sulphur .......................................itching or burning skin

Wyethia helenioides ............................congestion, cough

**“HPUS” indicates the active ingredients are in
the official Homeopathic Pharmacopeia of the
United States.